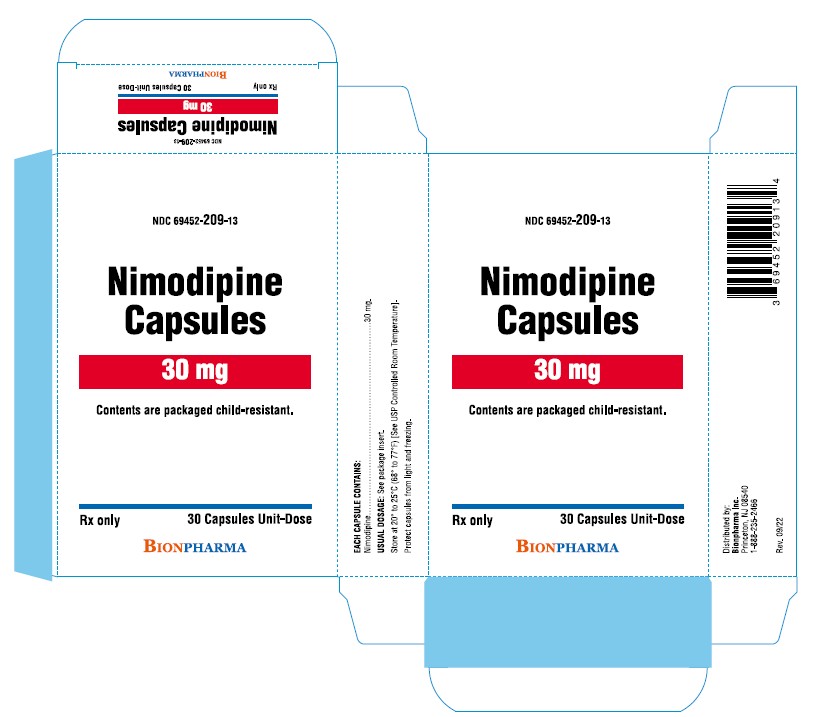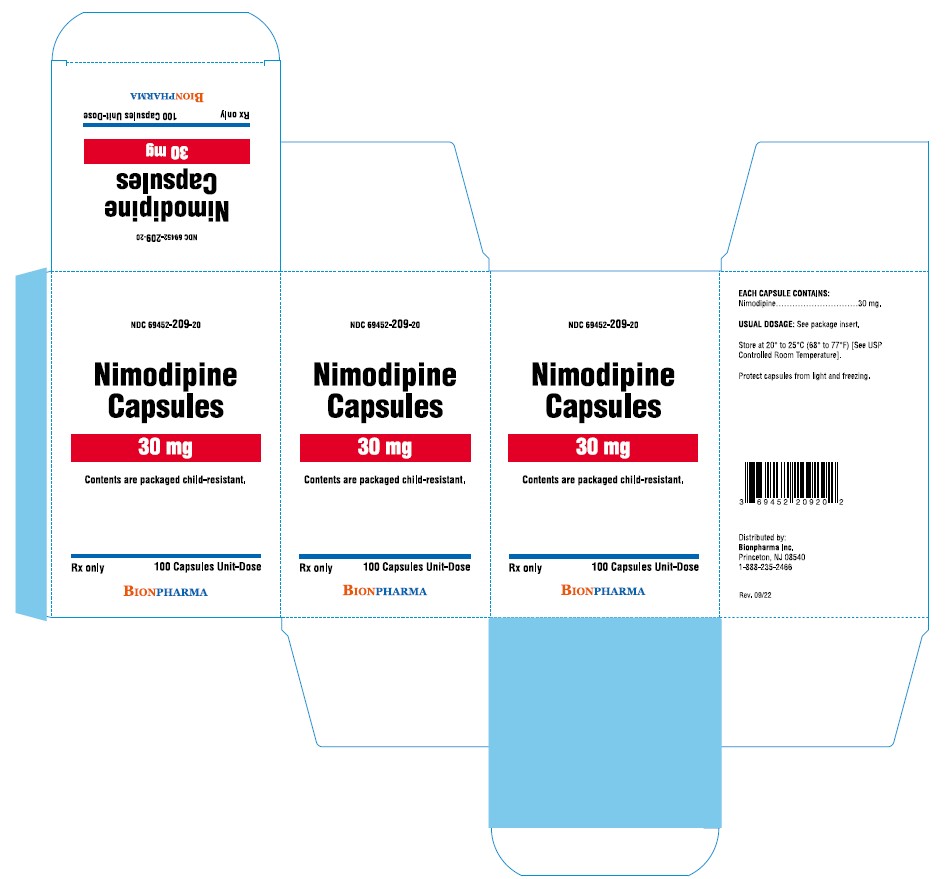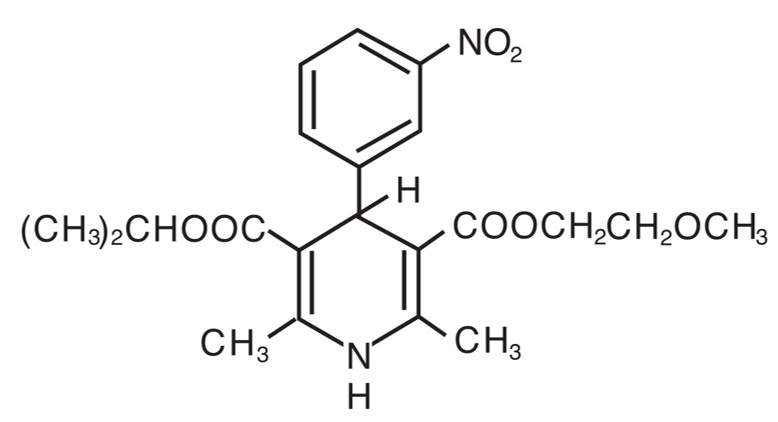 DRUG LABEL: Nimodipine
NDC: 69452-209 | Form: CAPSULE, LIQUID FILLED
Manufacturer: BIONPHARMA INC.
Category: prescription | Type: HUMAN PRESCRIPTION DRUG LABEL
Date: 20251204

ACTIVE INGREDIENTS: NIMODIPINE 30 mg/1 1
INACTIVE INGREDIENTS: GLYCERIN; FERROSOFERRIC OXIDE; HYPROMELLOSES; GELATIN; PEPPERMINT OIL; POLYETHYLENE GLYCOL, UNSPECIFIED; MANNITOL; PROPYLENE GLYCOL; SORBITOL; TITANIUM DIOXIDE

Nimodipine Capsules
For Oral Use
Rx only

BOXED WARNING

DO NOT ADMINISTER NIMODIPINE INTRAVENOUSLY OR BY OTHER PARENTERAL ROUTES. DEATHS AND SERIOUS, LIFE THREATENING ADVERSE EVENTS HAVE OCCURRED WHEN THE CONTENTS OF NIMODIPINE CAPSULES HAVE BEEN INJECTED PARENTERALLY (See WARNINGS and DOSAGE AND ADMINISTRATION).

DESCRIPTION

Nimodipine belongs to the class of pharmacological agents known as calcium channel blockers. Nimodipine is isopropyl 2 -methoxyethyl 1,4 –dihydro -2,6 –dimethyl -4-(m-nitrophenyl) -3,5-pyridinedicarboxylate. It has a molecular weight of 418.5 and a molecular formula of C21H26N2O7. The structural formula is:

Nimodipine is a yellow crystalline substance, practically insoluble in water.

Nimodipine capsules are formulated as soft gelatin capsules for oral administration. Each liquid filled capsule contains 30 mg of nimodipine. In addition the capsules contain the following inactive ingredients: gelatin, glycerin, hypromellose, iron oxide black, kosher glycerin, mannitol, peppermint oil, polyethylene glycol, propylene glycol, sorbitol, sorbitol anhydrides and titanium dioxide.

CLINICAL PHARMACOLOGY

Mechanism of Action

Nimodipine is a calcium channel blocker. The contractile processes of smooth muscle cells are dependent upon calcium ions, which enter these cells during depolarization as slow ionic transmembrane currents. Nimodipine inhibits calcium ion transfer into these cells and thus inhibits contractions of vascular smooth muscle. In animal experiments, nimodipine had a greater effect on cerebral arteries than on arteries elsewhere in the body perhaps because it is highly lipophilic, allowing it to cross the blood-brain barrier; concentrations of nimodipine as high as 12.5 ng/mL have been detected in the cerebrospinal fluid of nimodipine-treated subarachnoid hemorrhage (SAH) patients.

The precise mechanism of action of nimodipine in humans is unknown. Although the clinical studies described below demonstrate a favorable effect of nimodipine on the severity of neurological deficits caused by cerebral vasospasm following SAH, there is no arteriographic evidence that the drug either prevents or relieves the spasm of these arteries. However, whether or not the arteriographic methodology utilized was adequate to detect a clinically meaningful effect, if any, on vasospasm is unknown.

Pharmacokinetics and Metabolism

In man, nimodipine is rapidly absorbed after oral administration, and peak concentrations are generally attained within one hour. The terminal elimination half-life is approximately 8 to 9 hours but earlier elimination rates are much more rapid, equivalent to a half-life of 1 to 2 hours; a consequence is the need for frequent (every 4 hours) dosing. There were no signs of accumulation when nimodipine was given three times a day for seven days. Nimodipine is over 95% bound to plasma proteins. The binding was concentration independent over the range of 10 ng/mL to 10 μg/mL. Nimodipine is eliminated almost exclusively in the form of metabolites and less than 1% is recovered in the urine as unchanged drug. Numerous metabolites, all of which are either inactive or considerably less active than the parent compound, have been identified. The metabolism of nimodipine is mediated by CYP3A4. Because of a high first-pass metabolism, the bioavailability of nimodipine averages 13% after oral administration. The bioavailability is significantly increased in patients with hepatic cirrhosis, with Cmaxapproximately double that in normals which necessitates lowering the dose in this group of patients (see DOSAGE AND ADMINISTRATION). In a study of 24 healthy male volunteers, administration of nimodipine capsules following a standard breakfast resulted in a 68% lower peak plasma concentration and 38% lower bioavailability relative to dosing under fasted conditions.

In a single parallel-group study involving 24 elderly subjects (aged 59 to 79) and 24 younger subjects (aged 22 to 40), the observed AUC and Cmaxof nimodipine was approximately 2-fold higher in the elderly population compared to the younger study subjects following oral administration (given as a single dose of 30 mg and dosed to steady-state with 30 mg t.i.d. for 6 days). The clinical response to these age-related pharmacokinetic differences, however, was not considered significant. (See PRECAUTIONS, Geriatric Use.)

Clinical Trials

Nimodipine has been shown, in 4 randomized, double-blind, placebo-controlled trials, to reduce the severity of neurological deficits resulting from vasospasm in patients who have had a recent subarachnoid hemorrhage (SAH). The trials used doses ranging from 20 to 30 mg to 90 mg every 4 hours, with drug given for 21 days in 3 studies, and for at least 18 days in the other. Three of the four trials followed patients for 3 to 6 months. Three of the trials studied relatively well patients, with all or most patients in Hunt and Hess Grades I - III (essentially free of focal deficits after the initial bleed) the fourth studied much sicker patients, Hunt and Hess Grades III - V. Two studies, one U.S., one French, were similar in design, with relatively unimpaired SAH patients randomized to nimodipine or placebo. In each, a judgment was made as to whether any late-developing deficit was due to spasm or other causes, and the deficits were graded. Both studies showed significantly fewer severe deficits due to spasm in the nimodipine group; the second (French) study showed fewer spasm-related deficits of all severities. No effect was seen on deficits not related to spasm.

 |  |  |  | Patients
Study | Dose | Grade [Hunt and Hess Grade] |  | Number Analyzed | Any Deficit Due to Spasm | Numbers with Severe Deficit
U.S. | 20 to 30 mg | I-III | Nimodipine; Placebo | 56; 60 | 13; 16 | 1; 8 [p=0.03]
French | 60 mg | I-III | Nimodipine; Placebo | 31; 39 | 4; 11 | 2; 10

A third, large, study was performed in the United Kingdom in SAH patients with all grades of severity (but 89% were in Grades I-III). Nimodipine was dosed 60 mg every 4 hours. Outcomes were not defined as spasm related or not but there was a significant reduction in the overall rate of infarction and severely disabling neurological outcome at 3 months:

 | Nimodipine | Placebo
Total patients | 278 | 276
Good recovery | 199 [p = 0.0444 good and moderate vs severe and dead] | 169
Moderate disability | 24 | 16
Severe disability | 12 [p = 0.001 severe disability] | 31
Death | 43 [p = 0.056 death] | 60

A Canadian study entered much sicker patients, (Hunt and Hess Grades III-V), who had a high rate of death and disability, and used a dose of 90 mg every 4 hours, but was otherwise similar to the first two studies. Analysis of delayed ischemic deficits, many of which result from spasm, showed a significant reduction in spasm-related deficits. Among analyzed patients (72 nimodipine, 82 placebo), there were the following outcomes.

 | Delayed Ischemic Deficits; (DID) |  | Permanent Deficits
 | Nimodipine; n; (%) | Placebo n; (%) | Nimodipine; n; (%) | Placebo n; (%)
DID Spasm Alone | 8 (11) [p = 0.001, nimodipine vs placebo] | 25 (31) | 5 (7)* | 22 (27)
DID Spasm Contributing | 18 (25) | 21 (26) | 16 (22) | 17 (21)
DID Without Spasm | 7 (10) | 8 (10) | 6 (8) | 7 (9)
No DID | 39 (54) | 28 (34) | 45 (63) | 36 (44)

When data were combined for the Canadian and the United Kingdom studies, the treatment difference on success rate (i.e., good recovery) on the Glasgow Outcome Scale was 25.3% (nimodipine) versus 10.9% (placebo) for Hunt and Hess Grades IV or V. The table below demonstrates that nimodipine tends to improve good recovery of SAH patients with poor neurological status post-ictus, while decreasing the numbers with severe disability and vegetative survival.

Glasgow Outcome [p = 0.045, nimodipine vs placebo] | Nimodipine (n=87) |  | Placebo (n=101)
Good Recovery | 22 | (25.3%) | 11 | (10.9%)
Moderate Disability | 8 | (9.2%) | 12 | (11.9%)
Severe Disability | 6 | (6.9%) | 15 | (14.9%)
Vegetative Survival | 4 | (4.6%) | 9 | (8.9%)
Death | 47 | (54.0%) | 54 | (53.5%)

A dose-ranging study comparing 30, 60 and 90 mg doses found a generally low rate of spasm-related neurological deficits but no dose response relationship.

INDICATIONS AND USAGE

Nimodipine is indicated for the improvement of neurological outcome by reducing the incidence and severity of ischemic deficits in patients with subarachnoid hemorrhage from ruptured intracranial berry aneurysms regardless of their post-ictus neurological condition (i.e., Hunt and Hess Grades I-V).

CONTRAINDICATIONS

The concomitant use of nimodipine with strong inhibitors of CYP3A4 such as some macrolide antibiotics (e.g., clarithromycin, telithromycin), some anti-HIV protease inhibitors (e.g., delaviridine, indinavir, nelfinavir, ritonavir, saquinavir), some azole antimycotics (e.g., ketoconazole, itraconazole, voriconazole) and some antidepressants (e.g., nefazadone) is contraindicated because of a risk of significant hypotension (See PRECAUTIONS, Drug Interactions).

WARNINGS

DEATH DUE TO INADVERTENT INTRAVENOUS ADMINISTRATION: DO NOT ADMINISTER NIMODIPINE INTRAVENOUSLY OR BY OTHER PARENTERAL ROUTES. DEATHS AND SERIOUS, LIFE THREATENING ADVERSE EVENTS, INCLUDING CARDIAC ARREST, CARDIOVASCULAR COLLAPSE, HYPOTENSION, AND BRADYCARDIA, HAVE OCCURRED WHEN THE CONTENTS OF NIMODIPINE CAPSULES HAVE BEEN INJECTED PARENTERALLY (SEE DOSAGE AND ADMINISTRATION).

Reduced Efficacy with CYP3A4 Inducers:Concomitant use of strong CYP3A4 inducers (e.g. rifampin, phenobarbital, phenytoin, carbamazepine, St John’s wort) and nimodipine should generally be avoided, as nimodipine plasma concentration and efficacy may be very significantly reduced (see PRECAUTIONS, Drug Interactions).

Moderate and weak inducers of CYP3A4 may also reduce the efficacy of nimodipine to a lesser extent. Patients on these should be closely monitored for lack of effectiveness, and a nimodipine dosage increase may be required. Moderate and weak CYP3A4 inhibitors include, for example: amprenavir, aprepitant, armodafinil, bosentan, efavirenz, etravirine, echinacea, modafinil, nafcillin, pioglitazone, prednisone and rufinamide.

PRECAUTIONS

General

Blood Pressure: Nimodipine has the hemodynamic effects expected of a calcium channel blocker, although they are generally not marked. However, intravenous administration of the contents of nimodipine capsules has resulted in serious adverse consequences including death, cardiac arrest, cardiovascular collapse, hypotension, and bradycardia. In patients with subarachnoid haemorrhage given nimodipine in clinical studies, about 5% were reported to have had lowering of the blood pressure and about 1% left the study because of this (not all could be attributed to nimodipine). Nevertheless, blood pressure should be carefully monitored during treatment with nimodipine based on its known pharmacology and the known effects of calcium channel blockers. (see WARNINGSand DOSAGE AND ADMINISTRATION).

Hepatic Disease: The metabolism of nimodipine is decreased in patients with impaired hepatic function. Such patients should have their blood pressure and pulse rate monitored closely and should be given a lower dose (see DOSAGE AND ADMINISTRATION).

Intestinal pseudo-obstruction and ileus have been reported rarely in patients treated with nimodipine. A causal relationship has not been established. The condition has responded to conservative management.

Laboratory Test Interactions

None known.

Drug Interactions

Nimodipine is metabolized via the cytochrome P450 3A4 system located both in the intestinal mucosa and in the liver. Drugs that are known to either inhibit or to induce this enzyme system may therefore alter the first pass or the clearance of nimodipine.

In addition, the blood pressure lowering effects of antihypertensives could be enhanced when taken concomitantly with nimodipine.

Inducers of CYP3A4

Nimodipine plasma concentration and efficacy may be significantly reduced when concomitantly administered with strong CYP3A4 inducers. Therefore strong CYP3A4 inducers (e.g. rifampin, carbamazepine, phenobarbital, phenytoin, St. John’s Wort) should generally not be administered concomitantly with nimodipine (see WARNINGS).

Other moderate and weak inducers of CYP3A4 may also reduce the efficacy of nimodipine, although the magnitude of decrease in nimodipine plasma concentrations is not known. Patients on these should be closely monitored for lack of effectiveness, and a nimodipine dosage increase may be required. Moderate and weak CYP3A4 inducers include: amprenavir, aprepitant, armodafinil, bosentan, efavirenz, etravirine, Echinacea, modafinil, nafcillin, pioglitazone, prednisone and rufinamide.

Inhibitors of CYP3A4

Nimodipine plasma concentration can be significantly increased when concomitantly administered with strong inhibitors of the CYP3A4 system. As a consequence, the blood pressure lowering effect may be increased. Therefore strong CYP3A4 inhibitors should not be coadministered with nimodipine (See CONTRAINDICATIONS). Strong CYP3A4 inhibitors include some members of the following classes:

- macrolide antibiotics (e.g., clarithromycin, telithromycin,),

- HIV protease inhibitors (e.g., delavirdine, indinavir, nelfinavir, ritonavir, saquinavir),

- azole antimycotics (e.g., ketoconazole, itraconazole, voriconazole),

- antidepressants (e.g. nefazodone)

- grapefruit juice: after intake of grapefruit juice and nimodipine, the blood pressure lowering effect may last for at least 4 days after the last ingestion of grapefruit juice.

Ingestion of grapefruit / grapefruit juice is therefore not recommended while taking nimodipine (See DOSAGE AND ADMINISTRATION).

Nimodipine plasma concentration can also be increased in the presence of moderate and weak inhibitors of CYP3A4. If nimodipine is concomitantly administered with these drugs, blood pressure should be monitored, and a reduction of the nimodipine dose may be necessary. Moderate and weak CYP3A4 inhibitors include amprenavir, aprepitant, atazanavir, amiodarone, alprozalam, cyclosporine, cimetidine, erythromycin, fluconazole, fluoxetine, isoniazid, oral contraceptives, quinuprestin/dalforpristin, and valproic acid.

Blood pressure lowering drugs

Nimodipine may increase the blood pressure lowering effect of concomitantly administered anti-hypertensives, such as:

– diuretics,

– β-blockers,

– ACE inhibitors,

– A1-antagonists,

– other calcium antagonists,

– α-adrenergic blocking agents,

– PDE5 inhibitors,

– α-methyldopa.

Blood pressure should be carefully monitored, and dose adjustment of the blood pressure lowering drug(s) may be necessary.

Carcinogenesis, Mutagenesis, Impairment of Fertility

In a two-year study, higher incidences of adenocarcinoma of the uterus and Leydig-cell adenoma of the testes were observed in rats given a diet containing 1800 ppm nimodipine (equivalent to 91 to 121 mg/kg/day nimodipine) than in placebo controls. The differences were not statistically significant, however, and the higher rates were well within historical control range for these tumors in the Wistar strain. Nimodipine was found not to be carcinogenic in a 91-week mouse study but the high dose of 1800 ppm nimodipine-in-feed (546 to 774 mg/kg/day) shortened the life expectancy of the animals. Mutagenicity studies, including the Ames, micronucleus and dominant lethal tests were negative.

Nimodipine did not impair the fertility and general reproductive performance of male and female Wistar rats following oral doses of up to 30 mg/kg/day when administered daily for more than 10 weeks in the males and 3 weeks in the females prior to mating and continued to day 7 of pregnancy. This dose in a rat is about 4 times the equivalent clinical dose of 60 mg q4h in a 50 kg patient.

Pregnancy

Pregnancy Category C. Nimodipine has been shown to have a teratogenic effect in Himalayan rabbits. Incidences of malformations and stunted foetuses were increased at oral doses of 1 and 10 mg/kg/day administered (by gavage) from day 6 through day 18 of pregnancy but not at 3 mg/kg/day in one of two identical rabbit studies. In the second study an increased incidence of stunted fetuses was seen at 1 mg/kg/day but not at higher doses. Nimodipine was embryotoxic, causing resorption and stunted growth of fetuses, in Long Evans rats at 100 mg/kg/day administered by gavage from day 6 through day 15 of pregnancy. In two other rat studies, doses of 30 mg/kg/day nimodipine administered by gavage from day 16 of gestation and continued until sacrifice (day 20 of pregnancy or day 21 post partum) were associated with higher incidences of skeletal variatio n, stunted fetuses and stillbirths but no malformations. There are no adequate and well controlled studies in pregnant women to directly assess the effect on human fetuses. Nimodipine should be used during pregnancy only if the potential benefit justifies the potential risk to the fetus.

Nursing Mothers

Nimodipine and/or its metabolites have been shown to appear in rat milk at concentrations much higher than in maternal plasma. It is not known whether the drug is excreted in human milk. Because many drugs are excreted in human milk, nursing mothers are advised not to breast feed their babies when taking the drug.

Pediatric Use

Safety and effectiveness in children have not been established.

Geriatric Use

Clinical studies of nimodipine did not include sufficient numbers of subjects aged 65 and over to determine whether they respond differently from younger subjects. Other reported clinical experience has not identified differences in responses between the elderly and younger patients. In general, dosing in elderly patients should be cautious, reflecting the greater frequency of decreased hepatic, renal or cardiac function, and of concomitant disease or other drug therapy.

ADVERSE REACTIONS

Adverse experiences were reported by 92 of 823 patients with subarachnoid hemorrhage (11.2%) who were given nimodipine. The most frequently reported adverse experience was decreased blood pressure in 4.4% of these patients. Twenty-nine of 479 (6.1%) placebo treated patients also reported adverse experiences. The events reported with a frequency greater than 1% are displayed below by dose.

 | DOSE q4h Number of Patients (%) Nimodipine
Sign/Symptom | 0.35 mg/kg (n=82) | 30 mg (n=71) | 60 mg (n=494) | 90 mg (n=172) | 120 mg (n=4) | Placebo (n=479)
Decreased Blood Pressure | 1 (1.2) | 0 | 19 (3.8) | 14 (8.1) | 2 (50.0) | 6 (1.2)
Abnormal Liver Function Test | 1 (1.2) | 0 | 2 (0.4) | 1 (0.6) | 0 | 7 (1.5)
Edema | 0 | 0 | 2 (0.4) | 2 (1.2) | 0 | 3 (0.6)
Diarrhea | 0 | 3 (4.2) | 0 | 3 (1.7) | 0 | 3 (0.6)
Rash | 2 (2.4) | 0 | 3 (0.6) | 2 (1.2) | 0 | 3 (0.6)
Headache | 0 | 1 (1.4) | 6 (1.2) | 0 | 0 | 1 (0.2)
Gastrointestinal Symptoms | 2 (2.4) | 0 | 0 | 2 (1.2) | 0 | 0
Nausea | 1 (1.2) | 1 (1.4) | 6 (1.2) | 1 (0.6) | 0 | 0
Dyspnea | 1 (1.2) | 0 | 0 | 0 | 0 | 0
EKG Abnormalities | 0 | 1 (1.4) | 0 | 1 (0.6) | 0 | 0
Tachycardia | 0 | 1 (1.4) | 0 | 0 | 0 | 0
Bradycardia | 0 | 0 | 5 (1.0) | 1 (0.6) | 0 | 0
Muscle Pain/Cramp | 0 | 1 (1.4) | 1 (0.2) | 1 (0.6) | 0 | 0
Acne | 0 | 1 (1.4) | 0 | 0 | 0 | 0
Depression | 0 | 1 (1.4) | 0 | 0 | 0 | 0

There were no other adverse experiences reported by the patients who were given 0.35 mg/kg q4h, 30 mg q4h or 120 mg q4h. Adverse experiences with an incidence rate of less than 1% in the 60 mg q4h dose group were: hepatitis; itching; gastrointestinal hemorrhage; thrombocytopenia; anemia; palpitations; vomiting; flushing; diaphoresis; wheezing; phenytoin toxicity; lightheadedness; dizziness; rebound vasospasm; jaundice; hypertension; hematoma.

Adverse experiences with an incidence rate less than 1% in the 90 mg q4h dose group were: itching, gastrointestinal hemorrhage; thrombocytopenia; neurological deterioration; vomiting; diaphoresis; congestive heart failure; hyponatremia; decreasing platelet count; disseminated intravascular coagulation; deep vein thrombosis.

As can be seen from the table, side effects that appear related to nimodipine use based on increased incidence with higher dose or a higher rate compared to placebo control, included decreased blood pressure, edema and headaches which are known pharmacologic actions of calcium channel blockers. It must be noted, however, that SAH is frequently accompanied by alterations in consciousness which lead to an under reporting of adverse experiences. Patients who received nimodipine in clinical trials for other indications reported flushing (2.1%), headache (4.1%) and fluid retention (0.3%), typical responses to calcium channel blockers. As a calcium channel blocker, nimodipine may have the potential to exacerbate heart failure in susceptible patients or to interfere with A-V conduction, but these events were not observed.

No clinically significant effects on hematologic factors, renal or hepatic function or carbohydrate metabolism have been causally associated with oral nimodipine. Isolated cases of non-fasting elevated serum glucose levels (0.8%), elevated LDH levels (0.4%), decreased platelet counts (0.3%), elevated alkaline phosphatase levels (0.2%) and elevated SGPT levels (0.2%) have been reported rarely.

To report SUSPECTED ADVERSE REACTIONS, contact Bionpharma Inc. at 1-888-235-BION or 1-888-235-2466 or FDA at 1-800-FDA-1088 or www.fda.gov/medwatch.

DRUG ABUSE AND DEPENDENCE

There have been no reported instances of drug abuse or dependence with nimodipine

OVERDOSAGE

There have been no reports of overdosage from the oral administration of nimodipine. Symptoms of overdosage would be expected to be related to cardiovascular effects such as excessive peripheral vasodilation with marked systemic hypotension. Clinically significant hypotension due to nimodipine overdosage may require active cardiovascular support with pressor agents. Specific treatments for calcium channel blocker overdose should also be given promptly. Since nimodipine is highly protein-bound, dialysis is not likely to be of benefit.

DOSAGE AND ADMINISTRATION

DO NOT ADMINISTER NIMODIPINE CAPSULES INTRAVENOUSLY OR BY OTHER PARENTERAL ROUTES (see WARNINGS). If Nimodipine is inadvertently administered intravenously, clinically significant hypotension may require cardiovascular support with pressor agents. Specific treatments for calcium channel blocker overdose should also be given promptly.

Nimodipine is given orally in the form of soft gelatin 30 mg capsules for subarachnoid hemorrhage.

The recommended oral dose is 60 mg (two 30 mg capsules) every 4 hours for 21 consecutive days. In general, the capsules should be swallowed whole with a little liquid, preferably not less than one hour before or two hours after meals. Grapefruit juice is to be avoided (See PRECAUTIONS, Drug Interactions). Oral nimodipine therapy should commence as soon as possible within 96 hours of the onset of subarachnoid hemorrhage.

If the capsule cannot be swallowed, e.g., at the time of surgery, or if the patient is unconscious, a hole should be made in both ends of the capsule with an 18 gauge needle, and the contents of the capsule extracted into a syringe. A parenteral syringe can be used to extract the liquid inside the capsule, but the liquid should always be transferred to a syringe that cannot accept a needle and that is designed for administration orally or via a naso-gastric tube or PEG. To help minimize administration errors, it is recommended that the syringe used for administration be labeled “Not for IV Use”. The contents should then be emptied into the patient’s in situnaso-gastric tube and washed down the tube with 30 mL of normal saline (0.9%).

Severely disturbed liver function, particularly liver cirrhosis, may result in an increased bioavailability of nimodipine due to a decreased first pass capacity and a reduced metabolic clearance. The reduction in blood pressure and other adverse effects may be more pronounced in these patients. Dosage should be reduced to one 30 mg capsule every 4 hours with close monitoring of blood pressure and heart rate; if necessary, discontinuation of the treatment should be considered.

Strong inhibitors of CYP3A4 should not be administered concomitantly with nimodipine (See CONTRAINDICATIONS). Strong inducers of CYP3A4 should generally not be administered with nimodipine (See WARNINGS). Patients on moderate and weak inducers of CYP3A4 should be closely monitored for lack of effectiveness, and a nimodipine dose increase may be required. Patients on moderate and weak CYP3A4 inhibitors may require a nimodipine dose reduction in case of hypotension (See PRECAUTIONS, Drug Interactions).

HOW SUPPLIED

Nimodipine Capsules

30 mg - Oblong, white opaque, soft gelatin capsules in

Unit-Dose Package of 30 | NDC69452-209-13
Unit-Dose Package of 100 | NDC69452-209-20

Printed NM1 in black ink.

The capsules should be stored in the manufacturer’s original package.

Store at 20°to 25°C (68° to 77°F) [See USP Controlled Room Temperature].

Capsules should be protected from light and freezing.

Distributed by:

Bionpharma Inc.
Princeton, NJ 08540
Rev. 09/22

PACKAGE LABEL.PRINCIPAL DISPLAY PANEL

BIONPHARMA

NDC 69452-209-13

Nimodipine Capsules

30 mg

Contents are packaged child-resistant.

Rx only

30 Capsules Unit-Dose

PACKAGE LABEL

BIONPHARMA

NDC 69452-209-20

Nimodipine Capsules

30 mg

Contents are packaged child-resistant.

Rx only

100 Capsules Unit-Dose